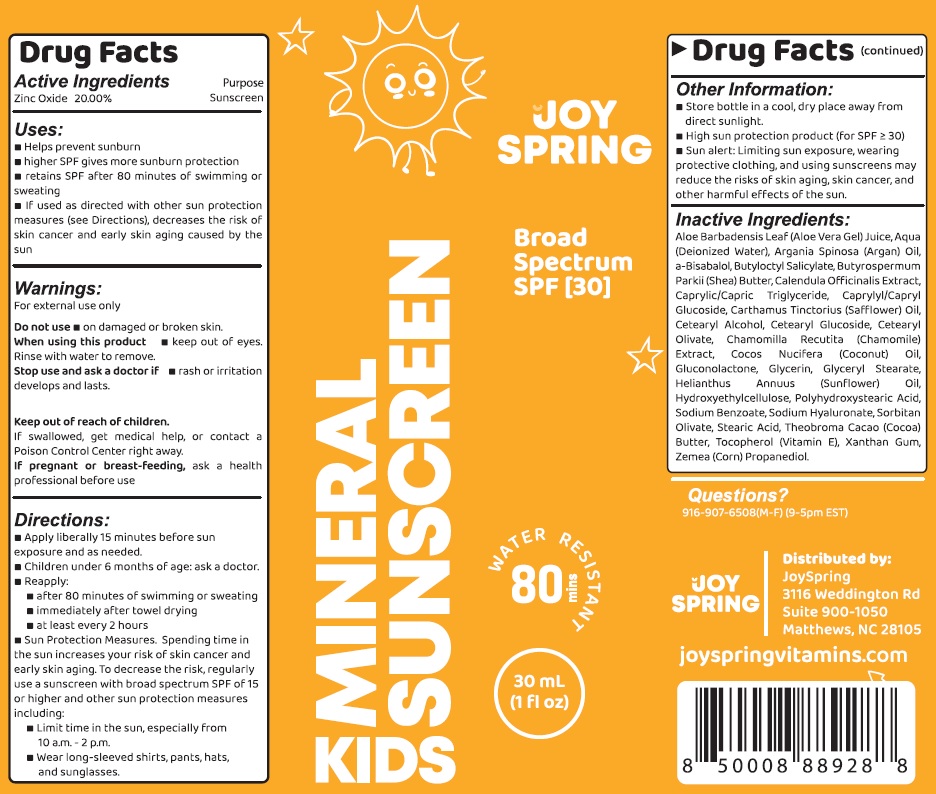 DRUG LABEL: JOYSPRING Kids Mineral Sunscreen SPF-30
NDC: 82552-354 | Form: CREAM
Manufacturer: JOYSPRING HOLDINGS LLC
Category: otc | Type: HUMAN OTC DRUG LABEL
Date: 20231111

ACTIVE INGREDIENTS: ZINC OXIDE 200 mg/1 mL
INACTIVE INGREDIENTS: ALOE VERA LEAF; WATER; ARGAN OIL; BUTYLOCTYL SALICYLATE; SHEA BUTTER; CALENDULA OFFICINALIS FLOWER; MEDIUM-CHAIN TRIGLYCERIDES; CAPRYLYL/CAPRYL OLIGOGLUCOSIDE; SAFFLOWER; CETOSTEARYL ALCOHOL; CETEARYL GLUCOSIDE; CETEARYL OLIVATE; CHAMOMILE; COCONUT OIL; GLUCONOLACTONE; GLYCERIN; GLYCERYL MONOSTEARATE; HELIANTHUS ANNUUS FLOWERING TOP; HYDROXYETHYL CELLULOSE, UNSPECIFIED; SODIUM BENZOATE; HYALURONATE SODIUM; SORBITAN OLIVATE; STEARIC ACID; COCOA; TOCOPHEROL; XANTHAN GUM; CORN

JOYSPRING Kids Mineral Sunscreen SPF-30

Active Ingredients

Zinc Oxide 20.00%

Purpose

Sunscreen

Uses:

- Helps prevent sunburn
- higher SPF gives more sunburn protection
- retains SPF after 80 minutes of swimming or sweating
- If used as directed with other sun protection measures (see Directions), decreases the risk of skin cancer and early skin aging caused by the sun

Warnings:

For external use only

Do not use

- on damaged or broken skin.

When using this product

- keep out of eyes. Rinse with water to remove.

Stop use and ask a doctor if

- rash or irritation develops and lasts.

Keep out of reach of children.

If swallowed, get medical help, or contact a Poison Control Center right away.

If pregnant or breast-Feeding,

ask a health professional before use

Directions:

- Apply liberally 15 minutes before sun exposure and as needed.
- Children under 6 months of age: ask a doctor
- Reapply:
- after 80 minutes of swimming or sweating
- immediately after towel drying
- at least every 2 hours
- Sun Protection measures. Spending time in the sun increases your risk of skin cancer and early skin aging. To decrease the risk, regularly use a sunscreen with broad spectrum SPF of 15 or higher and other sun protection measures including:
- Limit time in the sun, especially from 10 a.m. - 2 p.m.
- Wear long-sleeved shirts, pants, hats, and sunglasses.

Other Information:

- Store bottle in a cool, dry place away from direct sunlight.
- High sun protection product (for SPF > 30)
- Sun alert: Limiting sun exposure, wearing protective clothing, and using sunscreen may reduce the risks of skin aging, skin cancer, and other harmful effects of the sun.

Inactive Ingredients:

Aloe Barbadensis Leaf (Aloe Vera Gel) Juice, Aqua (Deionized Water), Argania Spinosa (Argan) Oil, a-Bisabalol,Butyloctyl Salicylate,Butyrospermum Parkii (Shea) Butter, Calendula Officinalis Extract, Caprylic/Capric Triglyceride, Caprylyl/Capryl GLucoside, Carthamus Tinctorius (Safflower) Oil, Cetearyl Alcohol, Cetearyl Glucoside, Cetearyl Olivate, Chamomilla Recutita (Chamomille) Extract, Cocos Nucifera (Coconut) Oil, Gluconolactone, Glycerin, Glyceryl Stearate, Helianthus Annuus (Sunflower) Oil, Hydroxyethylcellulose, Polyhydroxystearic Acid, Sodium Benzoate, Sodium Hyaluronate,Sorbitan Olivate, Stearic Acid, Theobroma Cacao (Cocoa) Butter, Tocopherol (Vitamin E), Xanthan Gum, Zemea (Corn) Propanediol.

Questions?

916-907-6508(M-F) (9-5pm EST)